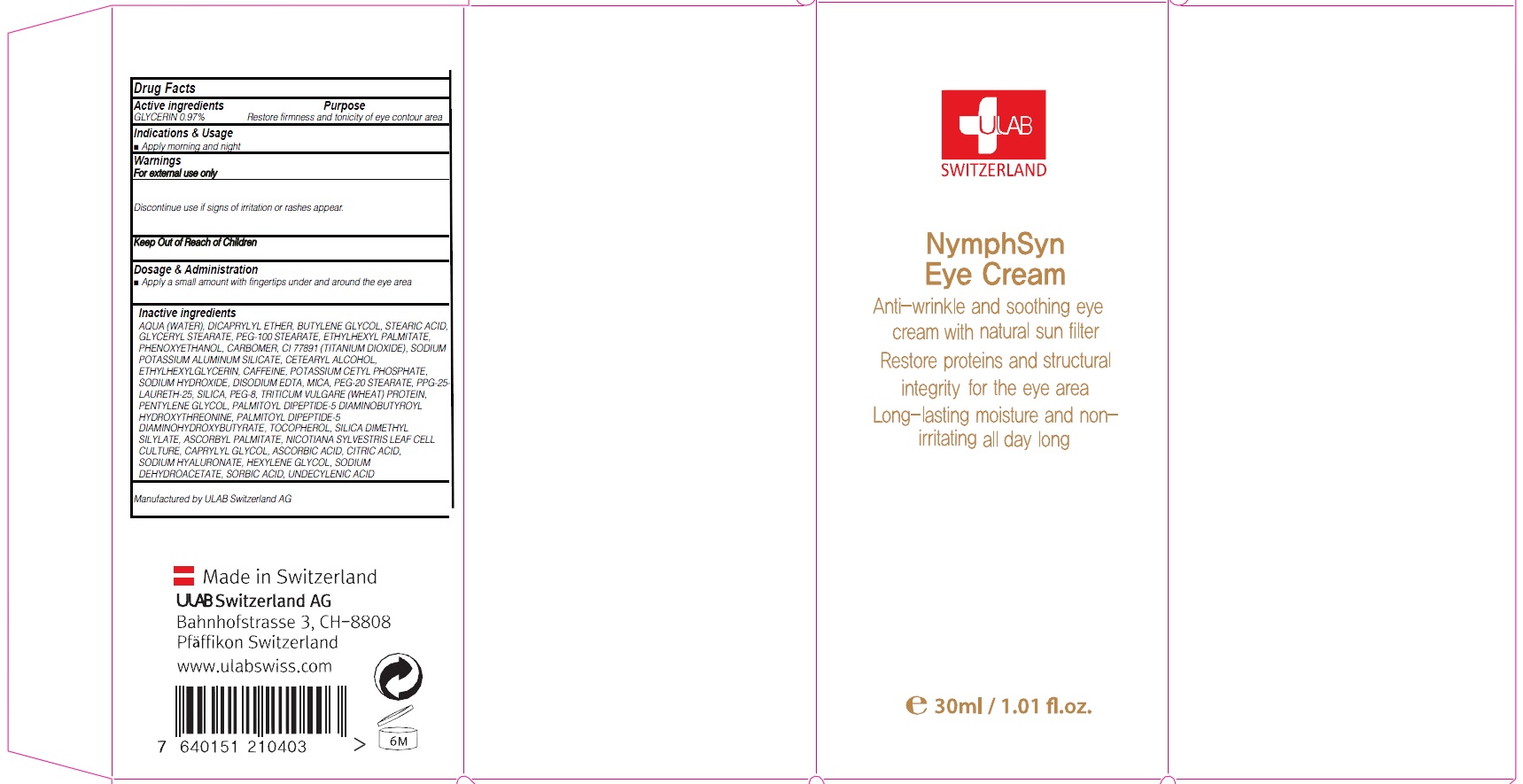 DRUG LABEL: NYMPHSYN EYE
NDC: 71276-040 | Form: CREAM
Manufacturer: ULAB
Category: otc | Type: HUMAN OTC DRUG LABEL
Date: 20170321

ACTIVE INGREDIENTS: GLYCERIN 0.29 g/30 mL
INACTIVE INGREDIENTS: WATER; DICAPRYLYL ETHER

ACTIVE INGREDIENT

Active ingredients: GLYCERIN 0.97%

INACTIVE INGREDIENT

Inactive ingredients: AQUA (WATER), DICAPRYLYL ETHER, BUTYLENE GLYCOL, STEARIC ACID, GLYCERYL STEARATE, PEG-100 STEARATE, ETHYLHEXYL PALMITATE, PHENOXYETHANOL, CARBOMER, CI 77891 (TITANIUM DIOXIDE), SODIUM POTASSIUM ALUMINUM SILICATE, CETEARYL ALCOHOL, ETHYLHEXYLGLYCERIN, CAFFEINE, POTASSIUM CETYL PHOSPHATE, SODIUM HYDROXIDE, DISODIUM EDTA, MICA, PEG-20 STEARATE, PPG-25-LAURETH-25, SILICA, PEG-8, TRITICUM VULGARE (WHEAT) PROTEIN, PENTYLENE GLYCOL, PALMITOYL DIPEPTIDE-5 DIAMINOBUTYROYL HYDROXYTHREONINE, PALMITOYL DIPEPTIDE-5 DIAMINOHYDROXYBUTYRATE, TOCOPHEROL, SILICA DIMETHYL SILYLATE, ASCORBYL PALMITATE, NICOTIANA SYLVESTRIS LEAF CELL CULTURE, CAPRYLYL GLYCOL, ASCORBIC ACID, CITRIC ACID, SODIUM HYALURONATE, HEXYLENE GLYCOL, SODIUM DEHYDROACETATE, SORBIC ACID, UNDECYLENIC ACID

PURPOSE

Purpose: Restore firmness and tonicity of eye contour area

WARNINGS

Warnings: For external use only Discontinue use if signs of irritation or rashes appear.

KEEP OUT OF REACH OF CHILDREN

INDICATIONS & USAGE

Indications & Usage: Apply morning and night

DOSAGE & ADMINISTRATION

Dosage & Administration: Apply a small amount with fingertips under and around the eye area